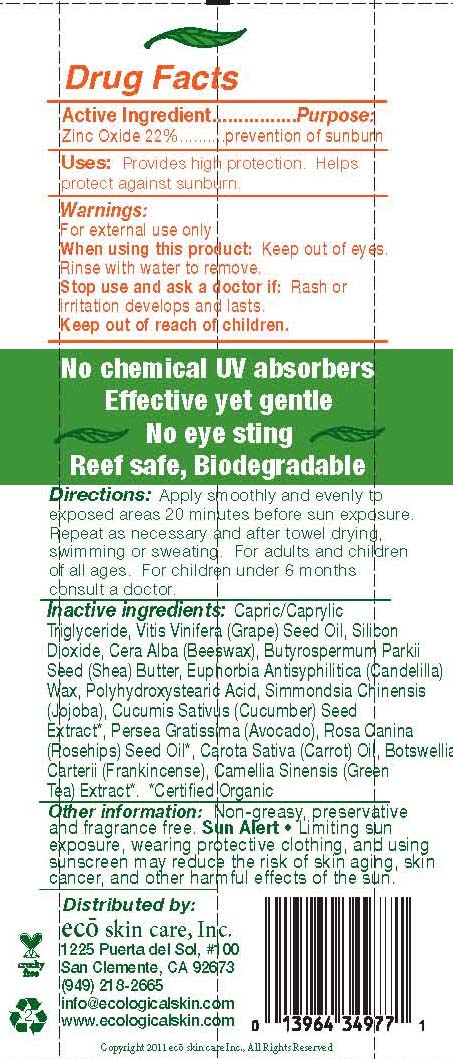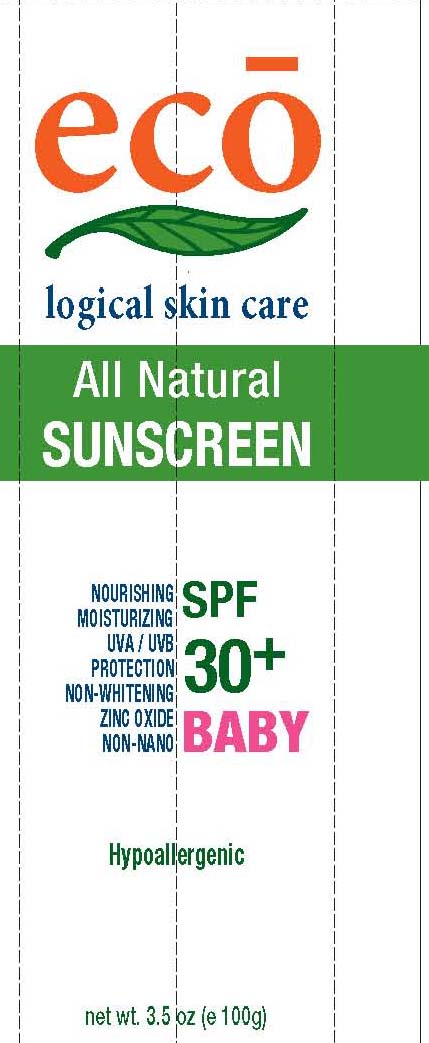 DRUG LABEL: Eco
NDC: 76105-479 | Form: LOTION
Manufacturer: Eco Skin Care
Category: otc | Type: HUMAN OTC DRUG LABEL
Date: 20110324

ACTIVE INGREDIENTS: Zinc Oxide 22 g/100 g
INACTIVE INGREDIENTS: GRAPE SEED OIL; SILICON DIOXIDE; SHEA BUTTER; CANDELILLA WAX; JOJOBA OIL; CUCUMBER SEED; Avocado

Eco Logicial Skin Care

Active Ingredient................Purpose:
Zinc Oxide 22%..........prevention of sunburn

PURPOSE

Provides high protection. Helps
protect against sunburn.

Keep out of reach of children.

INDICATIONS AND USAGE

For external use only

When using this product: Keep out of eyes.
Rinse with water to remove.
Stop use and ask a doctor if: Rash or
irritation develops and last

DOSAGE AND ADMINISTRATION

Apply smoothly and evenly to
exposed areas 20 minutes before sun exposure.
Repeat as necessary and after towel drying,
swimming or sweating. For adults and children
of all ages. For children under 6 months
consult a doctor

INACTIVE INGREDIENT

Capric/Caprylic Triglyceride, Vitis Vinifera (Grape) Seed Oil, Silicon
Dioxide, Cera Alba (Beeswax), Butyrospermum Parkii
Seed (Shea) Butter, Euphorbia Antisyphilitica (Candelilla)
Wax, Polyhydroxystearic Acid, Simmondsia Chinensis
(Jojoba), Cucumis Sativus (Cucumber) Seed
Extract*, Persea Gratissima (Avocado), Rosa Canina
(Rosehips) Seed Oil*, Carota Sativa (Carrot) Oil, Botswellia
Carterii (Frankincense), Camellia Sinensis (Green
Tea) Extract*. *Certified Organic

PACKAGE LABEL

eco logical skin care
all natural sunscreen
SPF 30
Baby
Hypoallergenic
3.5 oz (e 100g)